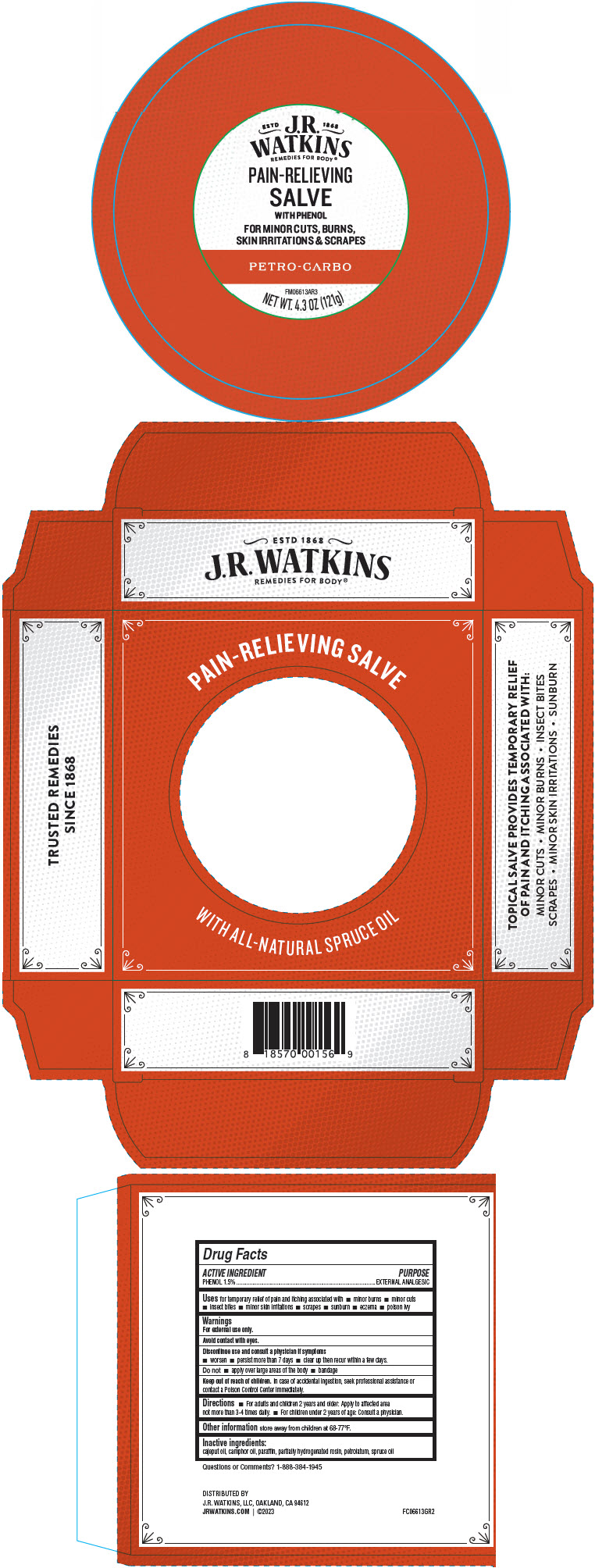 DRUG LABEL: Pain Relieving
NDC: 72342-060 | Form: SALVE
Manufacturer: J.R. Watkins, LLC.
Category: otc | Type: HUMAN OTC DRUG LABEL
Date: 20240206

ACTIVE INGREDIENTS: PHENOL 1.5 g/100 g
INACTIVE INGREDIENTS: PETROLATUM; PARAFFIN; ROSIN; CAJUPUT OIL; PICEA MARIANA LEAF OIL; CAMPHOR OIL

Pain Relieving Salve

Drug Facts

Active Ingredient

PHENOL 1.5%

Purpose

EXTERNAL ANALGESIC

Uses

for temporary relief of pain and itching associated with

- minor burns
- minor cuts
- insect bites
- minor skin irritations
- scrapes
- sunburn
- eczema
- poison ivy

Warnings

For external use only.

Avoid contact with eyes

Discontinue use and consult a physician if symptoms

- worsen
- persist for more than 7 days
- clear up the recur within a few days

Do not

- apply over large areas of the body
- bandage

Keep out of reach of children.In case of accidental ingestion, seek professional assistance or contact a Poison Control Center immediately.

Directions

- For adults and children 2 years and older: Apply to affected area not more than 3-4 times daily.
- For children under 2 years of age: Consult a physician.

Other information

store away from children at 68-77°F

Inactive ingredients

Cajeput oil, camphor oil, paraffin, partially hydrogenated rosin, petrolatum, spruce oil

Questions or Comments?

Call 1-888-384-1945

DISTRIBUTED BY
J.R. WATKINS, LLC, OAKLAND, CA 94612

PRINCIPAL DISPLAY PANEL - 121 g Jar Box

PAIN-RELIEVING SALVE

ESTD J.R. 1868
WATKINS
REMEDIES FOR BODY®

PAIN-RELIEVING
SALVE
WITH PHENOL

FOR MINOR CUTS, BURNS,
SKIN IRRITATIONS & SCRAPES

PETRO-CARBO

FM06613AR3

NET WT. 4.3 OZ (121g)

WITH ALL-NATURAL SPRUCE OIL